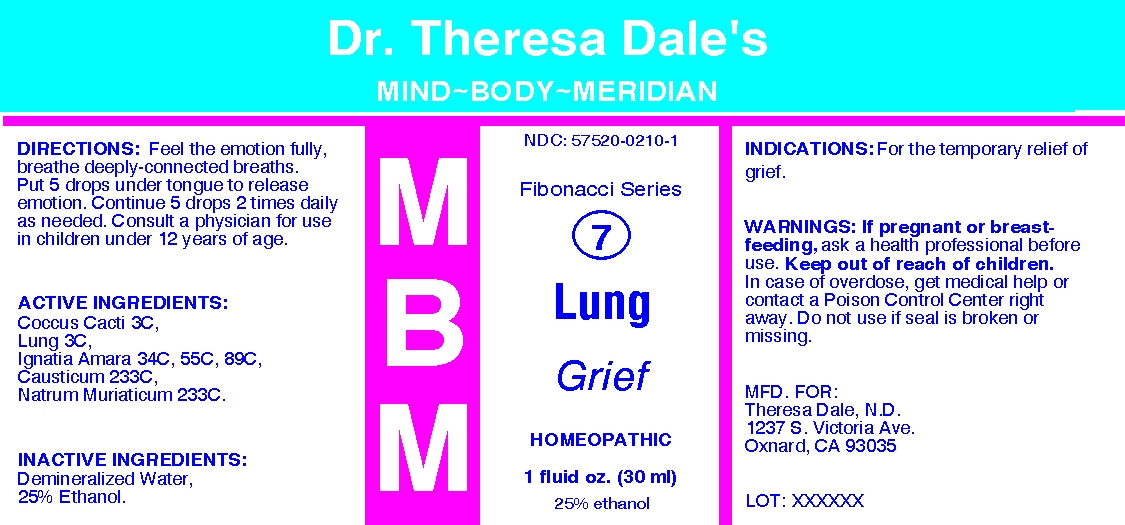 DRUG LABEL: MBM 7 Lung Grief
NDC: 57520-0210 | Form: LIQUID
Manufacturer: Apotheca Company
Category: homeopathic | Type: HUMAN OTC DRUG LABEL
Date: 20100723

ACTIVE INGREDIENTS: PROTORTONIA CACTI 3 [hp_C]/1 mL; STRYCHNOS IGNATII SEED 89 [hp_C]/1 mL; CAUSTICUM 233 [hp_C]/1 mL; SODIUM CHLORIDE 233 [hp_C]/1 mL; SUS SCROFA LUNG 3 [hp_C]/1 mL
INACTIVE INGREDIENTS: WATER; ALCOHOL

MBM 7 Lung Grief

ACTIVE INGREDIENT

ACTIVE INGREDIENTS: Coccus cacti 3C, Lung 3C, Ignatia amara 34C, 55C, 89C, Causticum 233C, Natrum muriaticum 233C.

PURPOSE

INDICATIONS: For the temporary relief of grief.

WARNINGS

WARNINGS: If pregnant or breast-feeding, ask a health professional before use.

Keep out of reach of children. In case of overdose, get medical help or contact a Poison Control Center right away.

Do not use if seal is broken or missing.

DOSAGE AND ADMINISTRATION

DIRECTIONS: Feel the emotion fully, breathe deeply-connected breaths. Put 5 drops under tongue to release emotion. Continue 5 drops 2 times daily as needed. Consult a physician for use in children under 12 years of age.

INACTIVE INGREDIENTS: Demineralized water, 25% Ethanol

QUESTIONS

MFD. FOR:

Theresa Dale, N.D.

1237 S Victoria Ave.

Oxnard, CA 93035

PACKAGE LABEL

Dr. Theresa Dale's

Mind-Body-Meridian

Fibonacci Series

7

LUNG

Grief

HOMEOPATHIC

1 fluid oz. (30 ml)